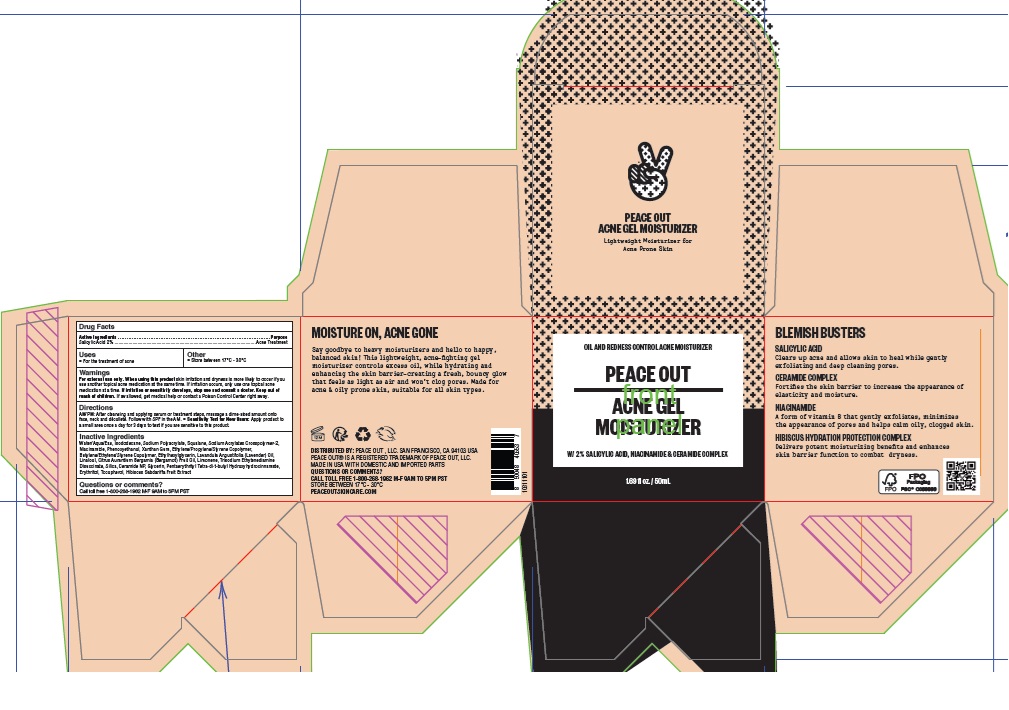 DRUG LABEL: Peace Out Acne Moisturizer
NDC: 71494-008 | Form: GEL
Manufacturer: Peace Out LLC.
Category: otc | Type: HUMAN OTC DRUG LABEL
Date: 20260129

ACTIVE INGREDIENTS: SALICYLIC ACID 20 mg/1 mL
INACTIVE INGREDIENTS: BERGAMOT OIL; XANTHAN GUM; TOCOPHEROL; WATER; LAVENDER OIL; ERYTHRITOL; PHENOXYETHANOL; LINALOOL, (+/-)-; ISODODECANE; LIMONENE, (+)-; TRISODIUM ETHYLENEDIAMINE DISUCCINATE; SILICON DIOXIDE; GLYCERIN; PENTAERYTHRITOL TETRAKIS(3-(3,5-DI-TERT-BUTYL-4-HYDROXYPHENYL)PROPIONATE); SODIUM POLYACRYLATE (2500000 MW); ETHYLHEXYLGLYCERIN; SQUALANE; SODIUM ACRYLATES CROSSPOLYMER-2; NIACINAMIDE; CERAMIDE NP; STYRENE/ISOPRENE COPOLYMER (28:72; 210000 MW)

Peace Out Acne Gel Moisturizer

Active Ingredients

Salicylic Acid 2%

Purpose

Acne Treatment

Uses

- For the treatment of acne

Other

- Store between 17C - 30C

Warnings

For external use only.

When using this product

skin irritation and dryness is more likely to occur if you use another topical acne medication at the same time. If irritation occurs, only use one topical acne medication at a time. If irritation or sensitivity develops, stop use and consult a doctor.

Keep out of reach of children.

If swallowed, get medical help or contact a Poison Control Center right away.

Directions

AM/PM: After cleansing and applying serum or treatment steps, massage a dime-sized amount onto face, neck and decollete. Follow with SPF in the A.M.

Sensitivity Test for New Users: Apply product to a small area once a day for 3 days to test if you are sensitive to this product.

Inactive Ingredients

Water/Aqua/Eau, Isododecane, Sodium Polyacrylate, Squalane, Sodium Acrylates Crosspolymer-2, Niacinamide, Phenoxyethanol, Xanthan Gum, Ethylene/Propylene/Styrene Copolymer, Butylene/Ethylene/Styrene Copolymer, Ethylhexylglycerin, Lavandula Angustifolia (Lavender) Oil, Linalool, Citrus Aurantium Bergamia (Bergamot) Fruit Oil, Limonene, Trisodium Ethylenediamine Disuccinate, Silica, Ceramide NP, Glycerin, Pentaerythrityl Tetra-di-t-butyl Hydroxyhydrocinnamate, Erythritol, Tocopherol, Hibiscus Sabdariffa Fruit Extract

Questions or comments?

Call toll free 1-800-268-1962 M-F 9AM to 5PM PST

Company Information

DISTRIBUTED BY: PEACE OUT, LLC. SAN FRANCISCO, CA 94103 USA

PEACEOUTSKINCARE.COM